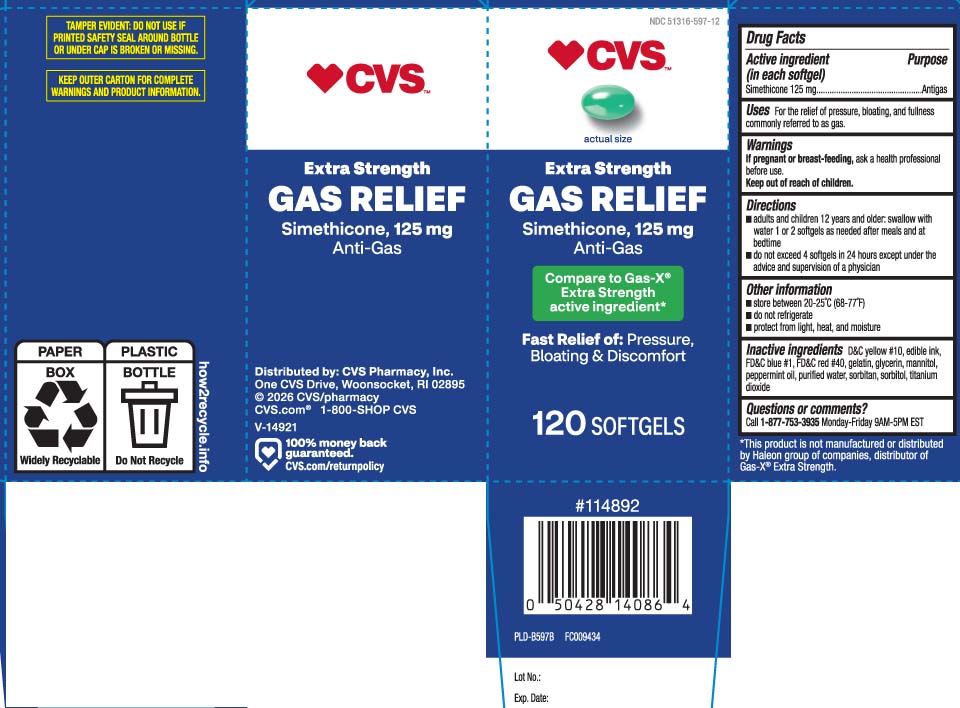 DRUG LABEL: Gas Relief
NDC: 51316-597 | Form: CAPSULE, LIQUID FILLED
Manufacturer: CVS PHARMACY, INC
Category: otc | Type: HUMAN OTC DRUG LABEL
Date: 20251217

ACTIVE INGREDIENTS: DIMETHICONE 125 mg/1 1
INACTIVE INGREDIENTS: D&C YELLOW NO. 10; FD&C BLUE NO. 1; FD&C RED NO. 40; GELATIN; GLYCERIN; PEPPERMINT OIL; WATER; SORBITAN; SORBITOL; TITANIUM DIOXIDE; MANNITOL

Drug Facts

Active ingredient (in each softgel)

Simethicone 125 mg

Purpose

Antigas

Uses

For the relief of pressure, bloating, and fullness commonly referred to as gas.

Warnings

If pregnant or breast-feeding,

ask a health professional before use.

Directions

- adults: swallow with water 1 or 2 softgels as needed after meals and at bedtime
- do not exceed 4 softgels in 24 hours except under the advice and supervision of a physician

Other information

- store between 20-25°C (68-77°F)
- do not refrigerate
- protect from light, heat, and moisture

Inactive ingredients

D&C yellow #10, edible ink, FD&C blue #1, FD&C red #40, gelatin, glycerin, mannitol, peppermint oil, purified water, sorbitan, sorbitol, titanium dioxide

Questions or comments?

Call 1-877-753-3935 Monday-Friday 9AM-5PM EST

Principal display panel

Compare to Gas-X® Extra Strength active ingredient*

Extra Strength

GAS RELIEF

Simethicone 125 mg

Anti-gas

Fast Relief of: Pressure, Bloating, Discomfort

SOFTGELS

*This product is not manufactured or distributed by Haleon group of companies, distributor of Gas-X® Extra Strength.

TAMPER EVIDENT: DO NOT USE IF PRINTED SAFETY SEAL AROUND BOTTLE OR UNDER CAP IS BROKEN OR MISSING

KEEP OUTER CARTON FOR COMPLETE WARNINGS AND PRODUCT INFORMATION.

Distributed by CVS Pharmacy, Inc.

One CVS Drive, Woonsocket, RI 02895

Product Label

CVS Extra Strength Gas Relief